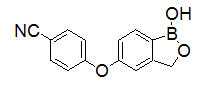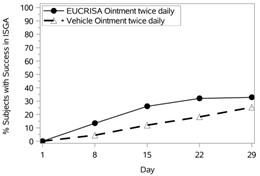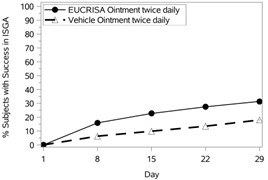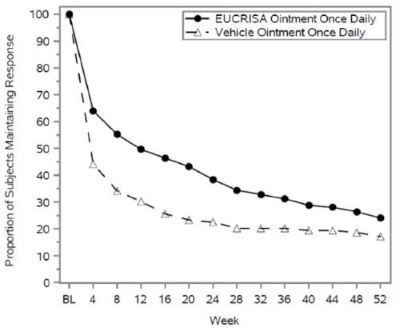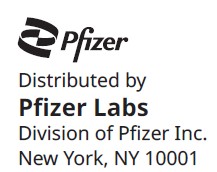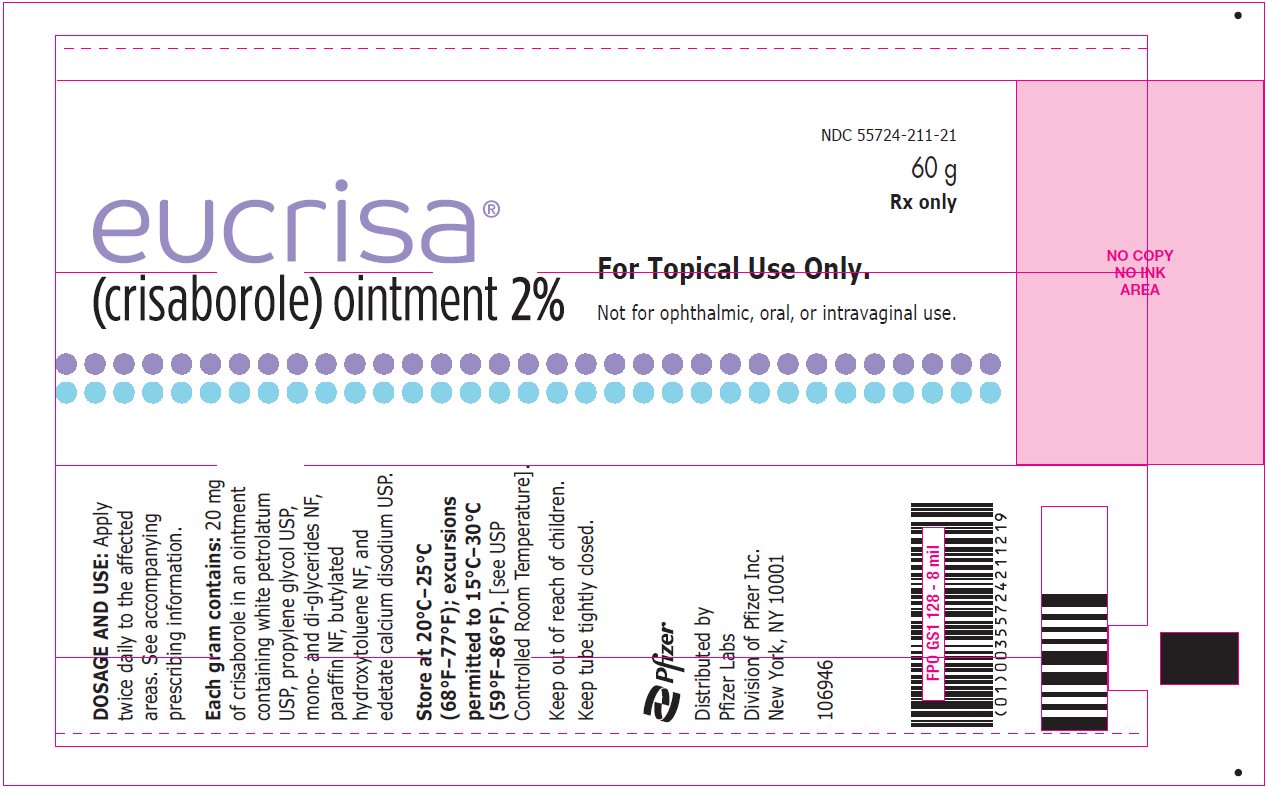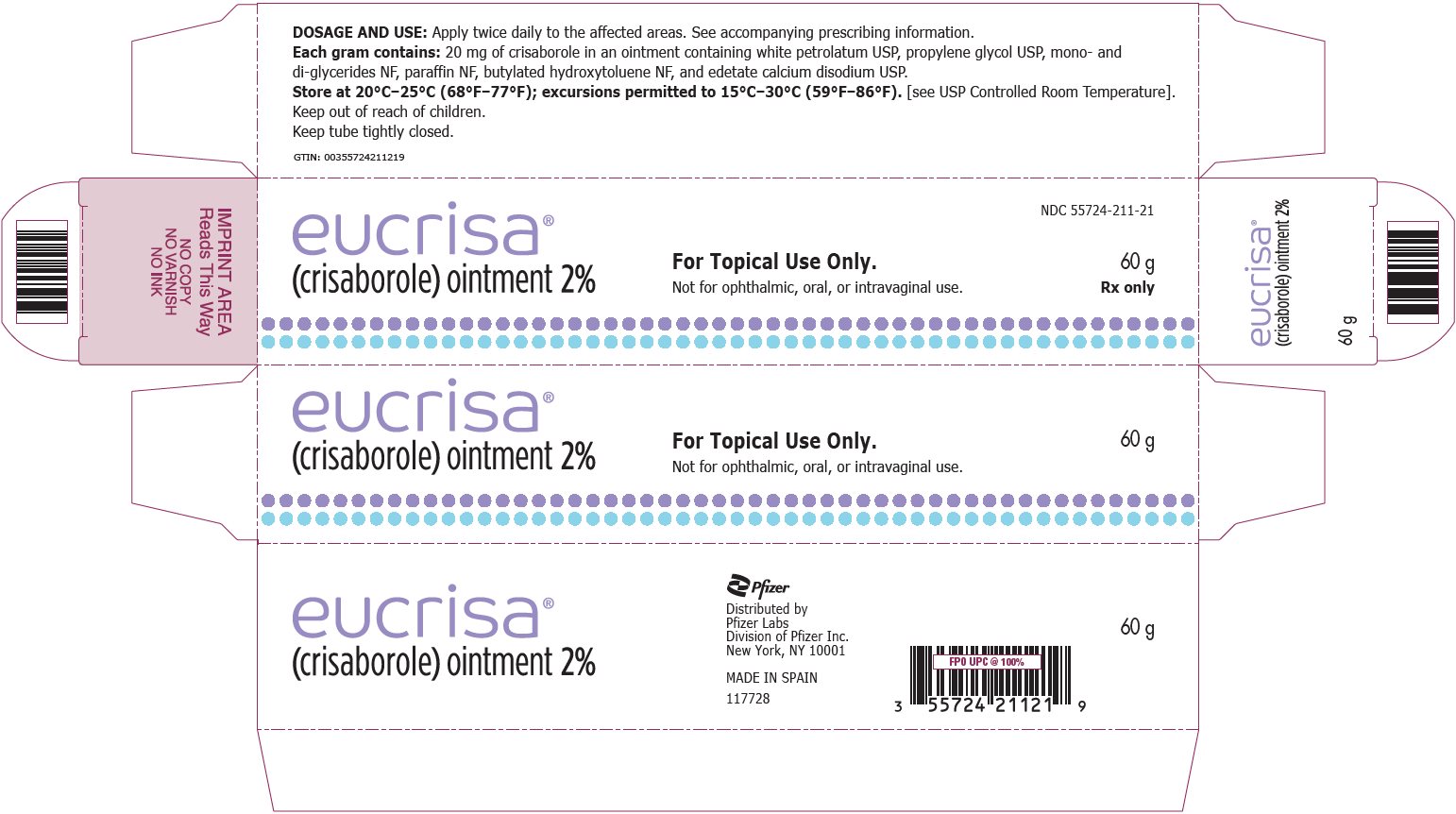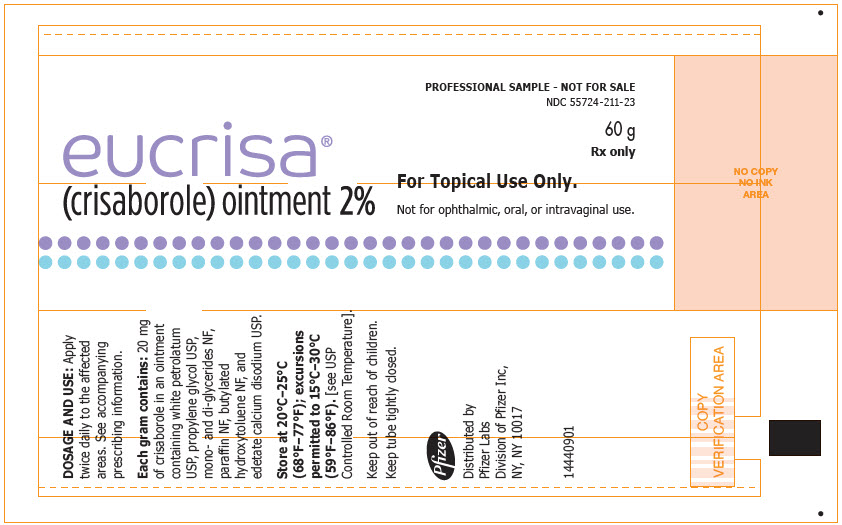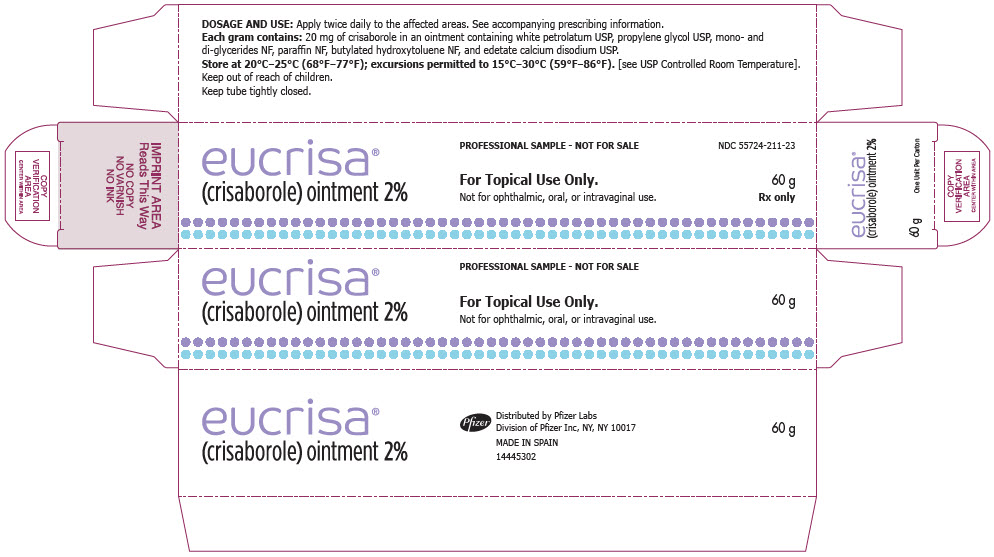 DRUG LABEL: Eucrisa
NDC: 55724-211 | Form: OINTMENT
Manufacturer: Pfizer Laboratories Div Pfizer Inc
Category: prescription | Type: HUMAN PRESCRIPTION DRUG LABEL
Date: 20250923

ACTIVE INGREDIENTS: CRISABOROLE 20 mg/1 g
INACTIVE INGREDIENTS: PETROLATUM; PROPYLENE GLYCOL; GLYCERYL MONOSTEARATE; PARAFFIN; BUTYLATED HYDROXYTOLUENE; EDETATE CALCIUM DISODIUM

HIGHLIGHTS OF PRESCRIBING INFORMATION

These highlights do not include all the information needed to use EUCRISA safely and effectively. See full prescribing information for EUCRISA.
EUCRISA® (crisaborole) ointment, for topical use
Initial U.S. Approval: 2016

1 INDICATIONS AND USAGE

EUCRISA is a phosphodiesterase 4 inhibitor indicated for topical treatment of mild to moderate atopic dermatitis in adult and pediatric patients 3 months of age and older. (1)

2 DOSAGE AND ADMINISTRATION

- Apply a thin layer twice daily to affected areas. (2)
- Once clinical effect is achieved, consider reducing application to once daily. (2)
- For topical use only. (2)
- Not for ophthalmic, oral, or intravaginal use. (2)

3 DOSAGE FORMS AND STRENGTHS

Ointment, 2%. (3)

4 CONTRAINDICATIONS

Known hypersensitivity to crisaborole or any component of the formulation. (4)

5 WARNINGS AND PRECAUTIONS

Hypersensitivity reactions: If signs and symptoms of hypersensitivity occur, discontinue EUCRISA immediately and initiate appropriate therapy. (5.1)

6 ADVERSE REACTIONS

The most common adverse reaction occurring in ≥1% in subjects is application site pain. (6.1)

To report SUSPECTED ADVERSE REACTIONS, contact Pfizer Inc. at 1-800-438-1985 or FDA at 1-800-FDA-1088 or www.fda.gov/medwatch.

FULL PRESCRIBING INFORMATION

1 INDICATIONS AND USAGE

EUCRISA is indicated for topical treatment of mild to moderate atopic dermatitis in adult and pediatric patients 3 months of age and older.

2 DOSAGE AND ADMINISTRATION

Apply a thin layer of EUCRISA twice daily to affected areas. Once clinical effect is achieved, consider reducing application to once daily [see Clinical Studies (14)].

EUCRISA is for topical use only and not for ophthalmic, oral, or intravaginal use.

3 DOSAGE FORMS AND STRENGTHS

Ointment: 20 mg of crisaborole per gram (2%) of white to off-white ointment.

4 CONTRAINDICATIONS

EUCRISA is contraindicated in patients with known hypersensitivity to crisaborole or any component of the formulation. [see Warnings and Precautions (5.1)]

5 WARNINGS AND PRECAUTIONS

5.1 Hypersensitivity Reactions

Hypersensitivity reactions, including contact urticaria, have occurred in patients treated with EUCRISA. Hypersensitivity should be suspected in the event of severe pruritus, swelling and erythema at the application site or at a distant site. If signs and symptoms of hypersensitivity occur, discontinue EUCRISA immediately and initiate appropriate therapy.

6 ADVERSE REACTIONS

6.1 Clinical Trials Experience

Because clinical trials are conducted under widely varying conditions, adverse reaction rates observed in the clinical trials of a drug cannot be directly compared to rates in the clinical trials of another drug and may not reflect the rates observed in practice.

In two double-blind, vehicle-controlled clinical trials (Trial 1 and Trial 2), 1012 subjects 2 to 79 years of age with mild to moderate atopic dermatitis were treated with EUCRISA twice daily for 4 weeks. The adverse reaction reported by ≥1% of EUCRISA-treated subjects is listed in Table 1.

Table 1: Adverse Reaction Occurring in ≥1% of Subjects in Atopic Dermatitis Trials through Week 4
Adverse Reaction | EUCRISA Twice Daily N=1012 n (%) | Vehicle Twice Daily N=499 n (%)
Application site pain [Refers to skin sensations such as burning or stinging.] | 45 (4) | 6 (1)

Less common (<1%) adverse reactions in subjects treated with EUCRISA included contact urticaria [see Warnings and Precautions (5.1)].

In one double-blind, vehicle-controlled trial including an initial open-label period (Trial 3), 497 subjects 3 months of age and older with mild to moderate atopic dermatitis received EUCRISA twice daily for up to 8 weeks. This was followed by a double-blind period, during which 135 subjects out of 270 randomized subjects received EUCRISA and 135 subjects received vehicle once daily for 52 weeks or until they developed a flare. The adverse reactions observed in the open-label period were similar to the known safety profile of twice daily treatment with EUCRISA. The adverse reactions observed with once daily treatment were similar to vehicle [see Clinical Studies (14)].

6.2 Postmarketing Experience

The following adverse reactions have been identified during postapproval use of EUCRISA. Because these reactions are reported voluntarily from a population of uncertain size, it is not always possible to reliably estimate their frequency or establish a causal relationship to drug exposure:

Skin and Subcutaneous: allergic contact dermatitis

8 USE IN SPECIFIC POPULATIONS

8.1 Pregnancy

Risk Summary

Available data from case reports with EUCRISA use in pregnant women are insufficient to inform a drug-associated risk for major birth defects, miscarriage, or other adverse maternal or fetal outcomes. In animal reproduction studies, there were no adverse developmental effects observed with oral administration of crisaborole in pregnant rats and rabbits during organogenesis at doses up to 3 and 2 times, respectively, the maximum recommended human dose (MRHD) (see Data).

The background risk of major birth defects and miscarriage for the indicated population is unknown. All pregnancies carry some risk of birth defect, loss, or other adverse outcomes. The background risk of major birth defects in the U.S. general population is 2% to 4% and of miscarriage is 15% to 20% of clinically recognized pregnancies.

Data

Animal Data

Rat and rabbit embryo-fetal development was assessed after oral administration of crisaborole. Crisaborole did not cause adverse effects to the fetus at oral doses up to 300 mg/kg/day in pregnant rats during the period of organogenesis (3 times the MRHD on an area under the curve (AUC) comparison basis). No crisaborole-related fetal malformations were noted after oral treatment with crisaborole in pregnant rats at doses up to 600 mg/kg/day (13 times the MRHD on an AUC comparison basis) during the period of organogenesis. Maternal toxicity was produced at this high dose of 600 mg/kg/day in pregnant rats and was associated with decreased fetal body weight and delayed skeletal ossification. Crisaborole did not cause adverse effects to the fetus at oral doses up to the highest dose tested of 100 mg/kg/day in pregnant rabbits during the period of organogenesis (2 times the MRHD on an AUC comparison basis).

In a prenatal/postnatal development study, pregnant rats were treated with crisaborole at doses of 150, 300, or 600 mg/kg/day by oral gavage during gestation and lactation (from gestation day 7 through day 20 of lactation). Crisaborole did not have any adverse effects on fetal development at doses up to 300 mg/kg/day (3 times the MRHD on an AUC comparison basis). Maternal toxicity was produced at the high dose of 600 mg/kg/day in pregnant rats and was associated with stillbirths, pup mortality, and reduced pup weights.

8.2 Lactation

Risk Summary

There is no information available on the presence of EUCRISA in human milk, the effects of the drug on the breastfed infant or the effects of the drug on milk production after topical application of EUCRISA to women who are breastfeeding. EUCRISA is systemically absorbed. The lack of clinical data during lactation precludes a clear determination of the risk of EUCRISA to a breastfed infant. Therefore, the developmental and health benefits of breastfeeding should be considered along with the mother's clinical need for EUCRISA and any potential adverse effects on the breastfed infant from EUCRISA or from the underlying maternal condition.

8.4 Pediatric Use

The safety and effectiveness of EUCRISA have been established in pediatric patients ages 3 months and older for topical treatment of mild to moderate atopic dermatitis. Use of EUCRISA administered twice daily in this age group is supported by data from two 28-day adequate, vehicle-controlled safety and efficacy trials (1,313 pediatric subjects ages 2 years to 17 years of whom 874 received EUCRISA), a 28-day open-label, safety and pharmacokinetics (PK) trial (137 subjects ages 3 months to less than 2 years who received EUCRISA), and another trial with an open-label period of up to 8 weeks (327 pediatric subjects ages 5 months to less than 18 years who received EUCRISA) [see Clinical Pharmacology (12.3) and Clinical Studies (14)].

The safety and effectiveness of EUCRISA in pediatric patients below the age of 3 months have not been established.

8.5 Geriatric Use

Clinical studies of EUCRISA did not include sufficient numbers of subjects age 65 and over to determine whether they respond differently from younger subjects.

11 DESCRIPTION

EUCRISA contains 2% crisaborole (w/w) in a petrolatum-based, white to off-white ointment and is for topical use. The active ingredient, crisaborole, is a phosphodiesterase-4 (PDE-4) inhibitor.

Crisaborole is described chemically as 5-(4-cyanophenoxy)-1,3-dihydro-1-hydroxy-[2,1]-benzoxaborole. The empirical formula is C14H10BNO3 and the molecular weight is 251.1 g/mol.

The structural formula is represented below:

Crisaborole drug substance is freely soluble in common organic solvents such as isopropyl alcohol and propylene glycol, and insoluble in water.

Each gram of EUCRISA contains 20 mg of crisaborole in an ointment containing white petrolatum, propylene glycol, mono- and di-glycerides, paraffin, butylated hydroxytoluene, and edetate calcium disodium.

12 CLINICAL PHARMACOLOGY

12.1 Mechanism of Action

Crisaborole is a phosphodiesterase 4 (PDE-4) inhibitor. PDE-4 inhibition results in increased intracellular cyclic adenosine monophosphate (cAMP) levels. The specific mechanism(s) by which crisaborole exerts its therapeutic action for the treatment of atopic dermatitis is not well defined.

12.2 Pharmacodynamics

Cardiac Electrophysiology

At therapeutic doses, EUCRISA ointment is not expected to prolong QTc to any clinically relevant extent.

12.3 Pharmacokinetics

Absorption

The PK of EUCRISA were investigated in 33 pediatric subjects 2 to 17 years of age with mild to moderate atopic dermatitis and a mean ± SD body surface area (BSA) involvement of 49 ± 20% (range 27% to 92%). In this study, subjects applied approximately 3 mg/cm^2 of EUCRISA ointment (dose range was approximately 6 g to 30 g per application) twice daily for 8 days.

Plasma concentrations were quantifiable in all the subjects. The mean ± SD maximum plasma concentration (Cmax) and area under the concentration time curve from 0 to 12 hours post dose (AUC0–12) for crisaborole on Day 8 were 127 ± 196 ng/mL and 949 ± 1240 ng h/mL, respectively. Systemic concentrations of crisaborole were at steady state by Day 8. Based on the ratios of AUC0–12 between Day 8 and Day 1, the mean accumulation factor for crisaborole was 1.9.

The PK of EUCRISA were investigated in 13 subjects 4 months to less than 24 months of age. The mean ± SD Cmax and AUC0–12 for crisaborole were 188 ± 100 ng/mL and 1164 ± 550 ng∙h/mL, respectively.

Distribution

Based on an in vitro study, crisaborole is 97% bound to human plasma proteins.

Elimination

Metabolism

Crisaborole is substantially metabolized into inactive metabolites. The major metabolite 5-(4-cyanophenoxy)-2-hydroxyl benzylalcohol (metabolite 1), is formed via hydrolysis; this metabolite is further metabolized into downstream metabolites, among which 5-(4-cyanophenoxy)-2-hydroxyl benzoic acid (metabolite 2), formed via oxidation, is also a major metabolite.

PK of metabolites 1 and 2 were assessed in the PK study described above and the systemic concentrations were at or near steady state by Day 8. Based on the ratios of AUC0–12 between Day 8 and Day 1, the mean accumulation factors for metabolites 1 and 2 were 1.7 and 6.3, respectively.

Excretion

Renal excretion of metabolites is the major route of elimination.

Drug Interaction Studies

In vitro studies using human liver microsomes indicated that under the conditions of clinical use, crisaborole and metabolite 1 are not expected to inhibit cytochrome P450 (CYP) 1A2, 2B6, 2C8, 2C9, 2C19, 2D6, and 3A4.

In vitro human liver microsomes studies for metabolite 2 showed that it did not inhibit activities of CYP2C19, 2D6, and 3A4; was a weak inhibitor of CYP1A2 and 2B6; and a moderate inhibitor of CYP2C8 and 2C9. The most sensitive enzyme, CYP2C9, was further investigated in a clinical trial using warfarin as a CYP2C9 substrate. The results of this study showed no drug interaction potential.

In vitro studies in human hepatocytes showed that under the conditions of clinical use, crisaborole and metabolites 1 and 2 are not expected to induce CYP enzymes.

In vitro studies showed that crisaborole and metabolite 1 did not inhibit the activities of uridine diphosphate (UDP)-glucuronosyltransferase (UGT) 1A1, 1A4, 1A6, 1A9, 2B7, and 2B15. Metabolite 2 did not inhibit UGT1A4, 1A6, 2B7, and 2B15. Metabolite 2 showed weak inhibition of UGT1A1, however, no clinically significant drug interactions are expected between crisaborole (and its metabolites) and UGT1A1 substrates at therapeutic concentrations. Metabolite 2 showed moderate inhibition of UGT1A9 and may result in a moderate increase of the concentrations of sensitive UGT1A9 substrates.

In vitro studies indicate that under the condition of clinical use, crisaborole and metabolites 1 and 2 are not expected to cause clinically significant interactions with substrates of P-glycoprotein and organic anionic or cationic transporters. Crisaborole and metabolite 1 are not expected to inhibit breast cancer resistance protein (BCRP); metabolite 2 is expected to inhibit BCRP at therapeutic concentrations.

13 NONCLINICAL TOXICOLOGY

13.1 Carcinogenesis, Mutagenesis, Impairment of Fertility

In an oral carcinogenicity study in Sprague-Dawley rats, oral doses of 30, 100, or 300 mg/kg/day crisaborole were administered to rats once daily. A crisaborole-related increased incidence of benign granular cell tumors in the uterus with cervix and vagina (combined) was noted in 300 mg/kg/day crisaborole treated female rats (2 times the MRHD on an AUC comparison basis). The clinical relevance of this finding is unknown.

In a dermal carcinogenicity study in CD-1 mice, topical doses of 2%, 5%, or 7% crisaborole ointment were administered once daily. No crisaborole-related neoplastic findings were noted at topical doses up to 7% crisaborole ointment (1 times the MRHD on an AUC comparison basis).

Crisaborole revealed no evidence of mutagenic or clastogenic potential based on the results of two in vitro genotoxicity tests (Ames assay and human lymphocyte chromosomal aberration assay) and one in vivo genotoxicity test (rat micronucleus assay).

No effects on fertility were observed in male or female rats that were administered oral doses up to 600 mg/kg/day crisaborole (13 times the MRHD on an AUC comparison basis) prior to and during early pregnancy.

14 CLINICAL STUDIES

Two multicenter, randomized, double-blind, parallel-group, vehicle-controlled trials (Trials 1 and 2) treated a total of 1522 subjects 2 to 79 years of age (86.3% of subjects were 2 to 17 years of age) with a 5% to 95% treatable BSA. At baseline, 38.5% of the subjects had an Investigator's Static Global Assessment [ISGA] of mild (2), and 61.5% had an ISGA of moderate (3), in the overall assessment of atopic dermatitis (erythema, induration/papulation, and oozing/crusting) on a severity scale of 0 to 4.

In both trials, subjects were randomized 2:1 to receive EUCRISA or vehicle applied twice daily for 28 days. The primary efficacy endpoint was the proportion of subjects at Day 29 who achieved success, defined as an ISGA grade of clear (0) or almost clear (1) with a 2-grade or greater improvement from baseline, comparing EUCRISA-treated subjects to vehicle-treated subjects.

Efficacy results from the two trials are summarized in Table 2.

Table 2: Primary Efficacy Outcomes in Subjects with Mild to Moderate Atopic Dermatitis at Day 29
 | Trial 1 |  | Trial 2
 | EUCRISA Twice Daily (N=503) | Vehicle Twice Daily (N=256) | EUCRISA Twice Daily (N=513) | Vehicle Twice Daily (N=250)
Success in ISGA [Defined as an ISGA of clear (0) or almost clear (1) with a 2-grade or greater improvement from baseline.] | 32.8% | 25.4% | 31.4% | 18.0%

The success rates over time are presented in Figure 1.

Figure 1: Success in ISGA [Success is defined as an ISGA of clear (0) or almost clear (1) with a 2-grade or greater improvement from baseline.] Over Time in Subjects with Mild to Moderate Atopic Dermatitis

Trial 1

Trial 2

One randomized, double-blind, vehicle-controlled trial (Trial 3) assessed the efficacy and safety of EUCRISA once daily over 52 weeks in pediatric (3 months to less than 18 years of age) and adult subjects with mild to moderate atopic dermatitis, who achieved success on EUCRISA twice daily during open-label treatment of up to 8 weeks.

A total of 497 subjects 3 months of age and older with a 2% to 90% treatable BSA, entered into an open-label period to receive EUCRISA twice daily for up to 8 weeks. At baseline, 327 (66%) of subjects were 3 months to less than 18 years of age, 66% of the subjects had an ISGA of moderate (3), and 34% had an ISGA of mild (2), in the overall assessment of atopic dermatitis (erythema, induration/papulation, and oozing/crusting) on a severity scale of 0 to 4.

Of the 497, a total of 254 subjects 3 months of age and older, who achieved both ISGA success (score of clear [0] or almost clear [1] with a ≥2 grade improvement from baseline) and EASI50 response (at least 50% improvement from baseline in EASI scores) were randomized 1:1 into a double-blind period to receive EUCRISA once daily or vehicle for 52 weeks or until they developed a flare. At the beginning of the double-blind period, 59% of the subjects had an ISGA of almost clear (1) and 41% had an ISGA of clear (0).

Figure 2 presents the percentage of subjects maintaining an ISGA of clear or almost clear through Week 52.

Figure 2: Percentage of Subjects Maintaining ISGA of Clear or Almost Clear Through Week 52

16 HOW SUPPLIED/STORAGE AND HANDLING

16.1 How Supplied

EUCRISA is a white to off-white ointment containing 2% crisaborole and is supplied in 60 g and 100 g laminate tubes.

60 g tube: NDC 55724-211-21
100 g tube: NDC 55724-211-11

16.2 Storage and Handling

Store at 20°C–25°C (68°F–77°F); excursions permitted to 15°C–30°C (59°F–86°F).
[see USP Controlled Room Temperature].

Keep tube tightly closed.

17 PATIENT COUNSELING INFORMATION

Advise the patient or caregivers to read the FDA-approved patient labeling (Patient Information).

Hypersensitivity Reactions

Advise patients to discontinue EUCRISA and seek medical attention immediately if signs or symptoms of hypersensitivity occur [see Warnings and Precautions (5.1)].

Administration Instructions

Advise patients or caregivers that EUCRISA is for topical use only and is not for ophthalmic, oral, or intravaginal use.

This product's labeling may have been updated. For the most recent prescribing information, please visit www.pfizer.com.

LAB-0916-6.0

PATIENT INFORMATION
EUCRISA® (you-KRIS-a)
(crisaborole) ointment

Important information: EUCRISA is for use on skin (topical use) only. Do not use EUCRISA in your eyes, mouth, or vagina.

What is EUCRISA?

EUCRISA is a prescription medicine used on the skin (topical) to treat mild to moderate eczema (atopic dermatitis) in adults and children 3 months of age and older.

It is not known if EUCRISA is safe and effective in children under 3 months of age.

Who should not use EUCRISA?

Do not use EUCRISA if you are allergic to crisaborole or any of the ingredients in EUCRISA. See the end of this Patient Information leaflet for a complete list of ingredients in EUCRISA.

Before using EUCRISA, tell your healthcare provider about all of your medical conditions, including if you:

- are pregnant or plan to become pregnant. It is not known if EUCRISA will harm your unborn baby.
- are breastfeeding or plan to breastfeed. It is not known if EUCRISA passes into your breast milk.

Tell your healthcare provider about all the medicines you take, including prescription and over-the-counter medicines, vitamins, and herbal supplements.

How should I use EUCRISA?

- Use EUCRISA exactly as your healthcare provider tells you to use it.
- Apply a thin layer of EUCRISA to the affected areas 2 times each day or as directed by your healthcare provider.
- Wash your hands after applying EUCRISA, unless hands are being treated. If someone else applies EUCRISA for you, they should wash their hands after applying EUCRISA.

What are the possible side effects of EUCRISA?

EUCRISA may cause side effects.

- Allergic reactions. EUCRISA may cause allergic reactions at or near the application site or at a distant site which may be serious. Stop using EUCRISA and get medical help right away if you have any symptoms of an allergic reaction including:

- trouble breathing or throat tightness

- hives

- chest tightness

- itching

- feeling faint
- swelling of your face, eyelids, lips, mouth, tongue or throat

- redness

The most common side effect of EUCRISA is application site pain, such as burning or stinging.

This is not the only possible side effect of EUCRISA.

Call your doctor for medical advice about side effects. You may report side effects to FDA at 1-800-FDA-1088.

How should I store EUCRISA?

- Store EUCRISA at room temperature, between 68°F to 77°F (20°C to 25°C).
- Keep the tube tightly closed.

Keep EUCRISA and all medicines out of the reach of children.

General information about the safe and effective use of EUCRISA

Medicines are sometimes prescribed for purposes other than those listed in a Patient Information leaflet. Do not use EUCRISA for a condition for which it was not prescribed. Do not give EUCRISA to other people, even if they have the same symptoms that you have. It may harm them. You can ask your pharmacist or healthcare provider for information about EUCRISA that is written for healthcare professionals.

What are the ingredients in EUCRISA?

Active ingredient: crisaborole

Inactive ingredients: white petrolatum, propylene glycol, mono- and di-glycerides, paraffin, butylated hydroxytoluene, and edetate calcium disodium.

LAB-0917-5.0

For more information, call 1-866-EUCRISA [1-866-382-7472] or go to www.EUCRISA.com

This Patient Information has been approved by the U.S. Food and Drug Administration.

Revised: 4/2023

PRINCIPAL DISPLAY PANEL - 60 g Tube Label

eucrisa®
(crisaborole) ointment 2%

NDC 55724-211-21
60 g
Rx only

For Topical Use Only.

Not for ophthalmic, oral, or intravaginal use.

PRINCIPAL DISPLAY PANEL - 60 g Tube Carton

eucrisa®
(crisaborole) ointment 2%

For Topical Use Only.
Not for ophthalmic, oral, or intravaginal use.

NDC 55724-211-21

60 g
Rx only

PRINCIPAL DISPLAY PANEL - 60 g Tube Label - Sample

eucrisa®
(crisaborole) ointment 2%

PROFESSIONAL SAMPLE - NOT FOR SALE
NDC 55724-211-23

60 g
Rx only

For Topical Use Only.

Not for ophthalmic, oral, or intravaginal use.

PRINCIPAL DISPLAY PANEL - 60 g Tube Carton - Sample

eucrisa®
(crisaborole) ointment 2%

PROFESSIONAL SAMPLE - NOT FOR SALE

For Topical Use Only.
Not for ophthalmic, oral, or intravaginal use.

NDC 55724-211-23

60 g
Rx only